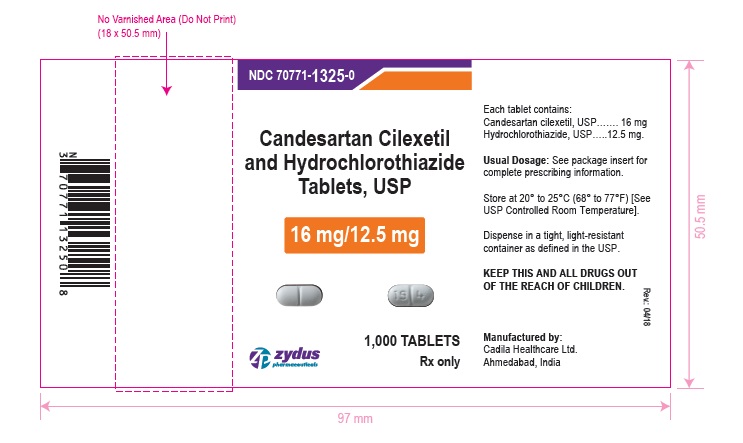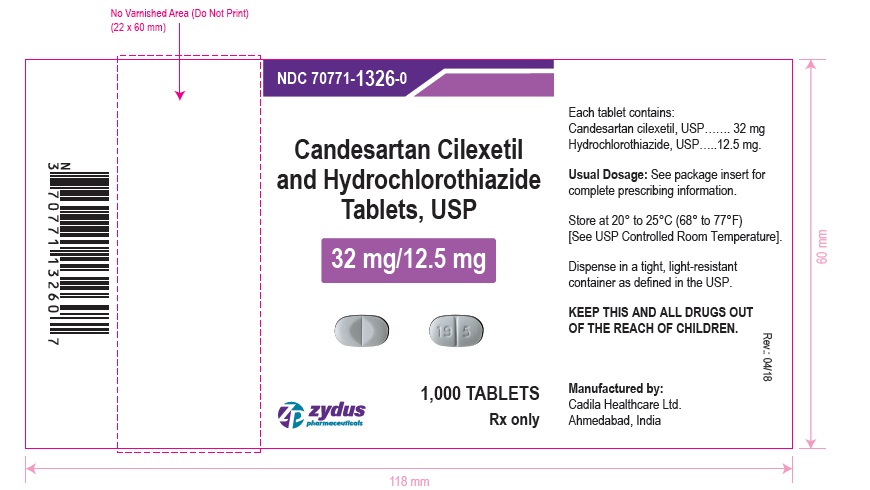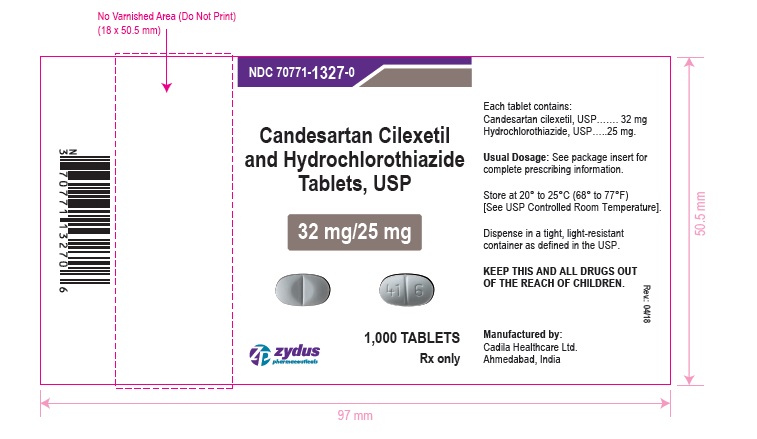 DRUG LABEL: candesartan cilexetil and hydrochlorothiazide
NDC: 70771-1325 | Form: TABLET
Manufacturer: Zydus Lifesciences Limited
Category: prescription | Type: HUMAN PRESCRIPTION DRUG LABEL
Date: 20241111

ACTIVE INGREDIENTS: CANDESARTAN CILEXETIL 16 mg/1 1; HYDROCHLOROTHIAZIDE 12.5 mg/1 1
INACTIVE INGREDIENTS: CARBOXYMETHYLCELLULOSE CALCIUM; STARCH, CORN; GLYCERYL MONO- AND DICAPRYLOCAPRATE; LACTOSE MONOHYDRATE; MAGNESIUM STEARATE; HYDROXYPROPYL CELLULOSE (110000 WAMW)

Candesartan Cilexetil and Hydrochlorothiazide Tablets USP, for oral use

PACKAGE LABEL.PRINCIPAL DISPLAY PANEL

NDC 70771-1325-0 in bottle of 1000 tablets

Candesartan Cilexetil and Hydrochlorothiazide Tablets USP, 16 mg/12.5 mg

Rx only

1000 tablets

NDC 70771-1326-0 in bottle of 1000 tablets

Candesartan Cilexetil and Hydrochlorothiazide Tablets USP, 32 mg/12.5 mg

Rx only

1000 tablets

NDC 70771-1327-0 in bottle of 1000 tablets

Candesartan Cilexetil and Hydrochlorothiazide Tablets USP, 32 mg/25 mg

Rx only

1000 tablets